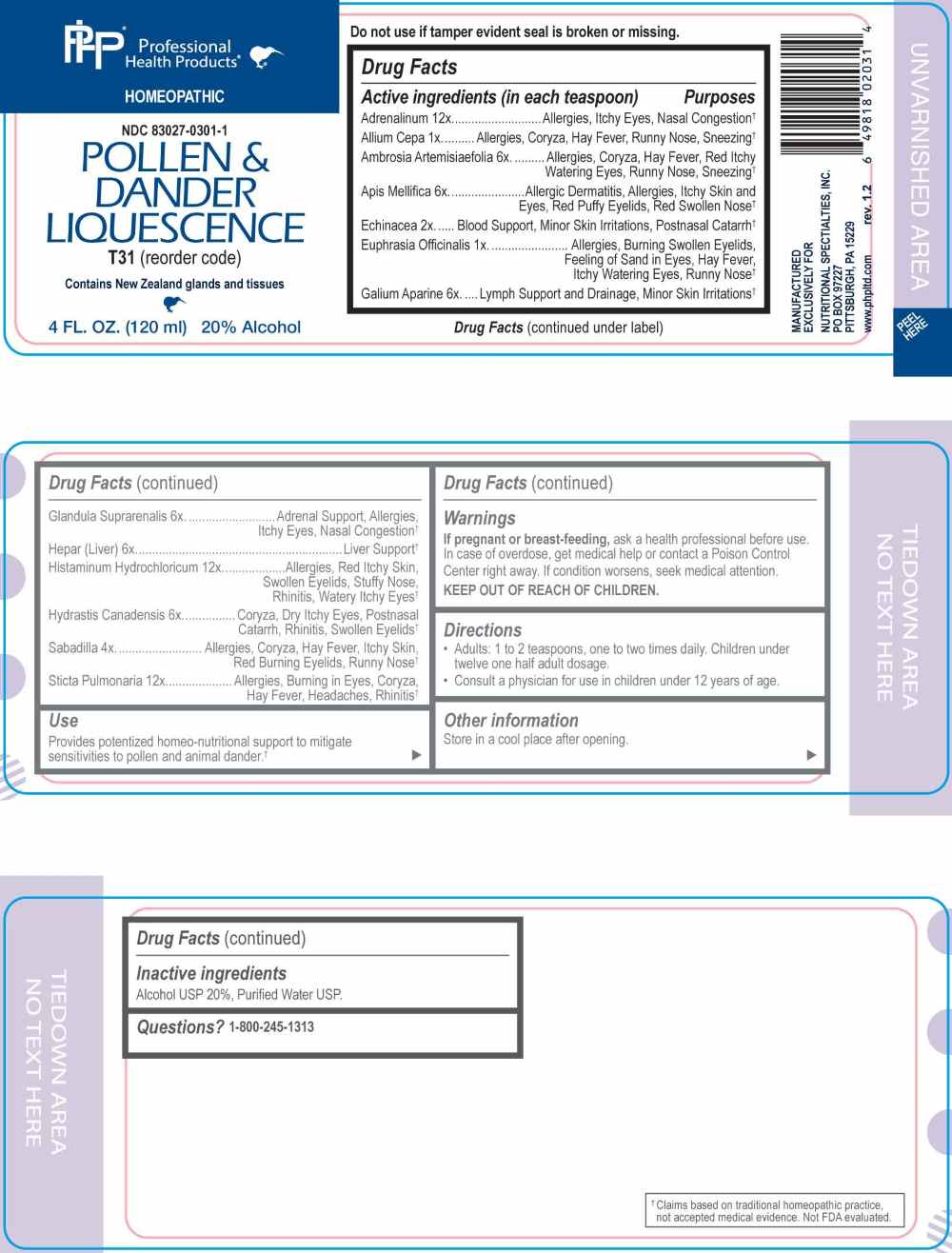 DRUG LABEL: Pollen and Dander Liquescence
NDC: 83027-0301 | Form: LIQUID
Manufacturer: Nutritional Specialties, Inc.
Category: homeopathic | Type: HUMAN OTC DRUG LABEL
Date: 20260223

ACTIVE INGREDIENTS: ONION 1 [hp_X]/1 mL; EUPHRASIA STRICTA 1 [hp_X]/1 mL; ECHINACEA ANGUSTIFOLIA WHOLE 2 [hp_X]/1 mL; SCHOENOCAULON OFFICINALE SEED 4 [hp_X]/1 mL; AMBROSIA ARTEMISIIFOLIA WHOLE 6 [hp_X]/1 mL; APIS MELLIFERA 6 [hp_X]/1 mL; GALIUM APARINE WHOLE 6 [hp_X]/1 mL; BOS TAURUS ADRENAL GLAND 6 [hp_X]/1 mL; BEEF LIVER 6 [hp_X]/1 mL; GOLDENSEAL 6 [hp_X]/1 mL; EPINEPHRINE 12 [hp_X]/1 mL; HISTAMINE DIHYDROCHLORIDE 12 [hp_X]/1 mL; LOBARIA PULMONARIA 12 [hp_X]/1 mL
INACTIVE INGREDIENTS: WATER; ALCOHOL

DRUG FACTS:

ACTIVE INGREDIENTS:

(in each teaspoon) Adrenalinum 12X, Allium Cepa 1X, Ambrosia Artemisiaefolia 6X, Apis Mellifica, Echinacea 2X, Euphrasia Officinalis 1X, Galium Aparine 6X, Glandula Suprarenalis 6X, Hepar (Liver) 6X, Histaminum Hydrochloricum 12X, Hydrastis Canadensis 6X, Sabadilla 4X, Sticta Pulmonaria 12X.

PURPOSE:

Adrenalinum – Allergies, Itchy Eyes, Nasal Congestion,† Allium Cepa – Allergies, Coryza, Hay Fever, Runny Nose, Sneezing,† Ambrosia Artemisiaefolia – Allergies, Coryza, Hay Fever, Red Itchy Watering Eyes. Runny Nose, Sneezing,† Apis Mellifica – Allergic Dermatitis, Allergies, Itchy Skin and Eyes, Red Puffy Eyelids, Red Swollen Nose,† Echinacea – Blood Support, Minor Skin Irritations, Postnasal Catarrh,† Euphrasia Officinalis – Allergies, Burning Swollen Eyelids, Feeling of Sand in Eyes, Hay Fever, Itchy Watering Eyes, Runny Nose,† Galium Aparine – Lymph Support and Drainage, Minor Skin Irritations,† Glandula Suprarenalis – Adrenal Support, Allergies, Itchy Eyes, Nasal Congestion,† Hepar (Liver) – Liver Support,† Histaminum Hydrochloricum – Allergies, Red Itchy Skin, Swollen Eyelids, Stuffy Nose, Rhinitis, Watery Itchy Eyes,† Hydrastis Canadensis – Coryza, Dry Itchy Eyes, Postnasal Catarrh, Rhinitis, Swollen Eyelids,† Sabadilla – Allergies, Coryza, Hay Fever, Itchy Skin, Red Burning Eyelids, Runny Nose,† Sticta Pulmonaria – Allergies, Buring in Eyes, Coryza, Hay Fever, Headaches, Rhinitis†

†Claims based on traditional homeopathic practice, not accepted medical evidence. Not FDA evaluated.

USES:

Provides potentized homeo-nutritional support to mitigate sensitivities to pollen and animal dander.†

†Claims based on traditional homeopathic practice, not accepted medical evidence. Not FDA evaluated.

WARNINGS:

If pregnant or breast-feeding, ask a health professional before use.

In case of overdose, get medical help or contact a Poison Control Center right away.

If condition worsens, seek medical attention.

KEEP OUT OF REACH OF CHILDREN

Do not use if tamper evident seal is broken or missing.

Store in a cool place after opening

KEEP OUT OF REACH OF CHILDREN:

In case of overdose, get medical help or contact a Poison Control Center right away.

DIRECTIONS:

• Adults 1 to 2 teaspoons one to two times daily. Children under twelve one half adult dosage.

• Consult a physician for use in children under 12 years of age.

INACTIVE INGREDIENTS:

Alcohol USP 20%, Purified Water USP.

QUESTIONS:

MANUFACTURED EXCLUSIVELY FOR

NUTRITIONAL SPECIALTIES, INC.

PO BOX 97227

PITTSBURG, PA 15229

www.phpltd.com

1-800-245-1313

PACKAGE LABEL DISPLAY:

Professional

Health Products

HOMEOPATHIC

NDC 83027-0301-1

POLLEN & DANDER

LIQUESCENCE

4 FL. OZ (120 ml)